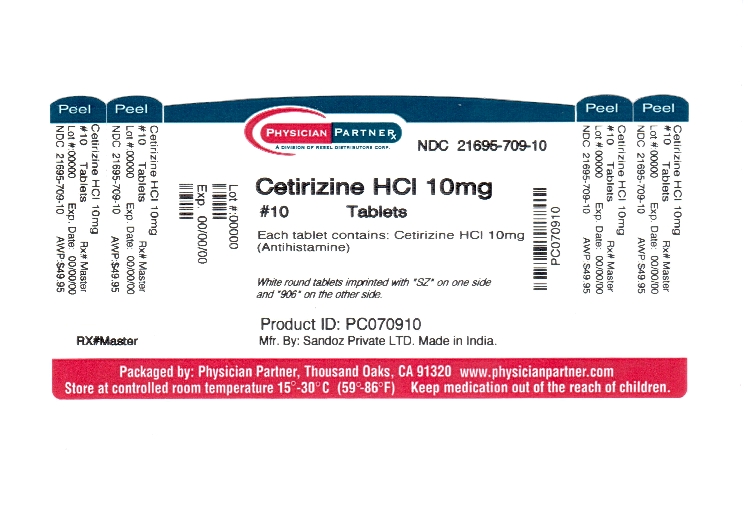 DRUG LABEL: Cetirizine Hydrochloride
NDC: 21695-709 | Form: TABLET
Manufacturer: Rebel Distributors Corp
Category: otc | Type: HUMAN OTC DRUG LABEL
Date: 20110209

ACTIVE INGREDIENTS: CETIRIZINE HYDROCHLORIDE 10 mg/1 1
INACTIVE INGREDIENTS: STARCH, CORN; HYPROMELLOSES; LACTOSE MONOHYDRATE; MAGNESIUM STEARATE; POVIDONE; TITANIUM DIOXIDE; POLYETHYLENE GLYCOLS

Cetirizine Drug Facts

Active ingredient

(in each tablet)

Cetirizine HCl 10 mg

Purpose

Antihistamine

Keep out of reach of children

In case of overdose, get medical help or contact a Poison Control Center right away.

Uses

Temporarily relieves these symptoms due to hay fever or other upper respiratory allergies:

- runny nose
- sneezing
- itchy, watery eyes
- itching of the nose or throat

Warnings

Do not use if you have ever had an allergic reactions to this product or any of its ingredients or to an antihistamine containing hydroxyzine.

Ask a doctor before use if you have liver or kidney disease. Your doctor should determine if you need a different dose.

Ask a doctor or pharmacist before use if you are taking tranquilizers or sedatives.

When using this product

- drowsiness may occur
- avoid alcoholic drinks
- alcohol, sedatives, and tranquilizers may increase drowsiness
- be careful when driving a motor vehicle or operating machinery

Stop use and ask a doctor if an allergic reaction to this product occurs. Seek medical help right away.

If pregnant or breast-feeding:

- if breast-feeding: not recommended
- if pregnant: ask a health professional before use.

Directions

adults and children 6 years and over | One 10 mg tablet once daily; do not take more than one 10 mg tablet in 24 hours. A 5 mg product may be appropriate for less severe symptoms.
adults 65 years and over | ask a doctor
children under 6 years of age | ask a doctor
consumers with liver or kidney disease | ask a doctor

Other information

Store between 20 to 25 C (68 to 77 F)

Inactive ingredients

Corn starch, hypromellose, lactose monohydrate, macrogol, magnesium stearate, povidone and titanium dioxide.

Questions? 1-800-525-8747

Manufactured in India by Sandoz Private Ltd.,

for Sandoz Inc., Princeton, NJ 08540

Rev.02/2008

Repackaged by:

Rebel Distributors Corp

Thousand Oaks, CA 91320

Principal Display Panel

NDC 21695-709-10 Bottle of 10

NDC 21695-709-14 Bottle of 14

NDC 21695-709-20 Bottle of 20

NDC 21695-709-30 Bottle of 30

Cetirizine HCl Tablets

10 mg

antihistamine

Do not use if individual blister unit is open or torn

ALLERGY

Indoor & Outdoor Allergies

24 hour Relief of

- Sneezing
- Runny Nose
- Itchy, Watery Eyes
- Itchy Throat or Nose